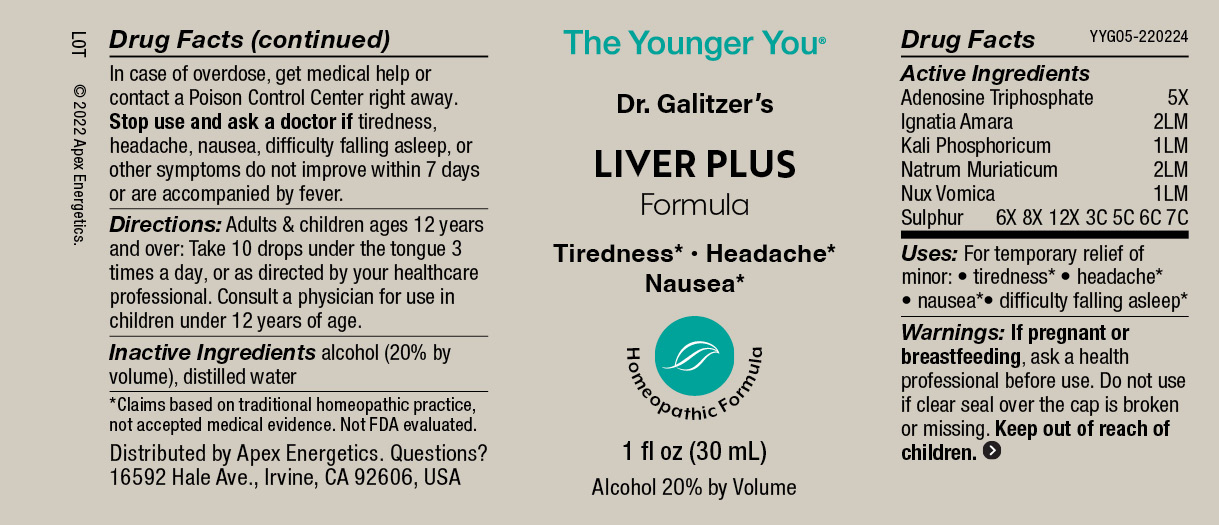 DRUG LABEL: LIVER PLUS Formula
NDC: 63479-2505 | Form: SOLUTION/ DROPS
Manufacturer: Apex Energetics Inc.
Category: homeopathic | Type: HUMAN OTC DRUG LABEL
Date: 20240108

ACTIVE INGREDIENTS: ADENOSINE TRIPHOSPHATE 5 [hp_X]/1 mL; STRYCHNOS IGNATII SEED 2 [hp_Q]/1 mL; DIBASIC POTASSIUM PHOSPHATE 1 [hp_Q]/1 mL; SODIUM CHLORIDE 2 [hp_Q]/1 mL; STRYCHNOS NUX-VOMICA SEED 1 [hp_Q]/1 mL; SULFUR 7 [hp_C]/1 mL
INACTIVE INGREDIENTS: ALCOHOL; WATER

YYG05

Active Ingredients
Adenosine Triphosphate | 5X
Ignatia Amara | 2LM
Kali Phosphoricum | 1LM
Natrum Muriaticum | 2LM
Nux Vomica | 1LM
Sulphur | 6X 8X 12X 3C 5C 6C 7C

INDICATIONS AND USAGE

Uses:

For temporary relief of minor:

tiredness*

headache*

nausea*

difficulty falling asleep*

*Claims based on traditional homeopathic practice, not accepted medical evidence. Not FDA evaluated.

Warnings:

PREGNANCY OR BREAST FEEDING

If pregnant or breastfeeding, ask a health professional before use.

Do not use if clear seal over the cap is broken or missing.

Keep out of reach of children. In case of overdose, get medical help or contact a Poison Control Center right away.

Stop use and ask a doctor if tiredness, headache, nausea, difficulty falling asleep, or other symptoms do not improve within 7 days or are accompanied by fever.

Directions:

Adults & children ages 12 years and over: Take 10 drops under the tongue 3 times a day, or as directed by your healthcare professional. Consult a physician for use in children under 12 years of age.

Inactive Ingredients

alcohol (20% by volume), distilled water

Distributed by Apex Energetics. Questions?

16592 Hale Ave., Irvine, CA 92606, USA

PACKAGE LABEL

The Younger You®

Dr. Galitzer’s

LIVER PLUS
Formula

Tiredness* Headache*

Nausea*

Homeopathic Formula

1 fl oz (30 mL)

Alcohol 20% by Volume